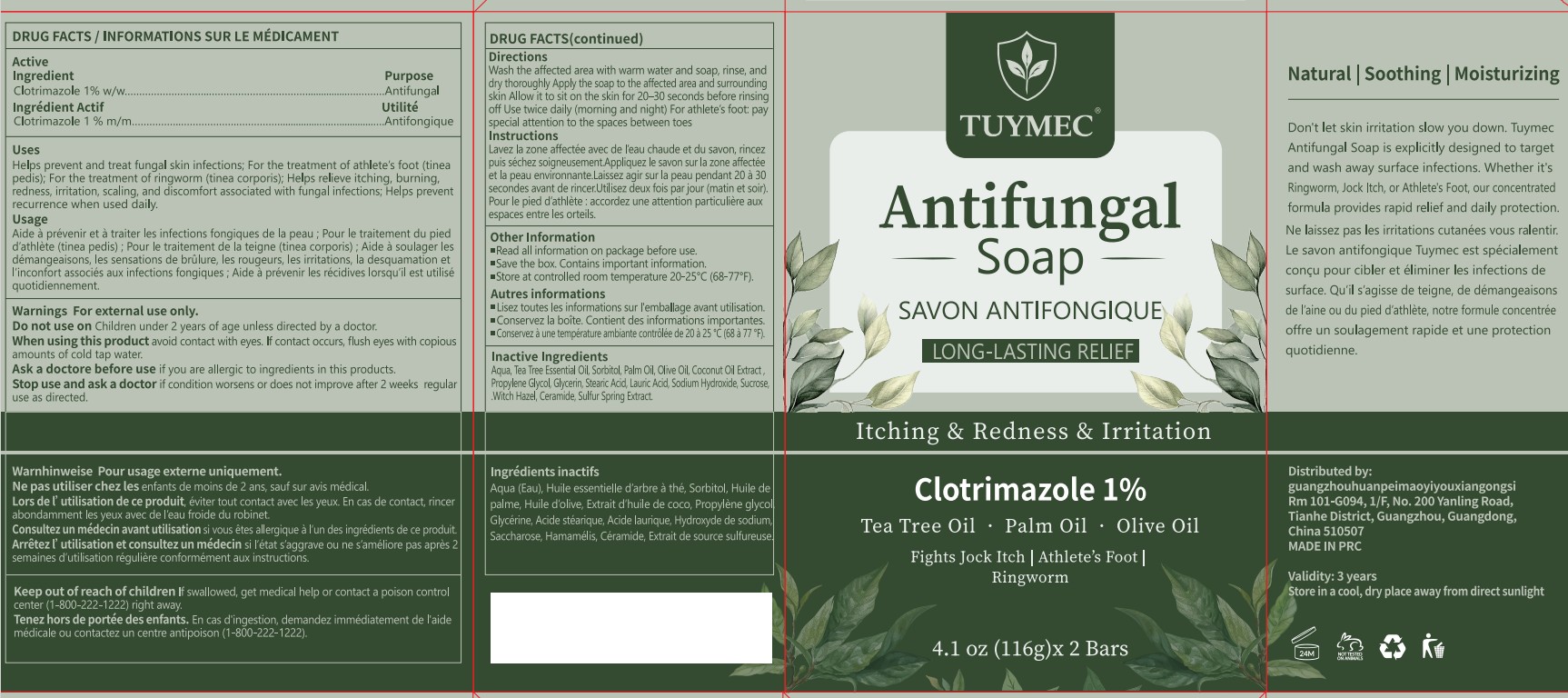 DRUG LABEL: Tuymec Antifungal Medicated Bar
NDC: 87408-003 | Form: SOAP
Manufacturer: Guangzhou Jingliang Cosmetics Co., Ltd.
Category: otc | Type: HUMAN OTC DRUG LABEL
Date: 20260211

ACTIVE INGREDIENTS: CLOTRIMAZOLE 1 g/100 g
INACTIVE INGREDIENTS: WITCH HAZEL; CERAMIDE NP; SUCROSE; LAURIC ACID; SODIUM HYDROXIDE; SULFUR; AQUA; SORBITOL; PALM OIL; OLIVE OIL; COCONUT OIL; PROPYLENE GLYCOL; GLYCERIN; STEARIC ACID; TEA TREE OIL

Active Ingredient

Active ingredient: Clotrimazole 1%

Ask a doctor before use

if you are allergic to ingredients in this product

Do not use

on Children under 2 years of age unless directed by a doctor.

Keep Oot Of Reach Of Children

If swallowed, get medical help or contact a poison control center (1-800-222-1222) right away.

Purpose

Antifungal

Stop use and ask a doctor

if condition worsens or does not improve after 2 weeks regular use as directed.

When Using

When using this product avoid contact with eyes. If contact occurs, flush eyes with copious amounts of cold tap water.

Directions

Wash the affected area with warm water and soap, rinse, and dry thoroughly

Apply the soap to the affected area and surrounding skin

Allow it to sit on the skin for 20–30 seconds before rinsing off

Use twice daily (morning and night)

For athlete’s foot: pay special attention to the spaces between toes

Inactive ingredients

Aqua, Tea Tree Essential Oil, Sorbitol, Palm Oil, Olive Oil, Coconut Oil Extract ,Propylene Glycol, Glycerin, Stearic Acid, Lauric Acid, Sodium Hydroxide, Sucrose, .Witch Hazel, Ceramide, Sulfur Spring Extract.

Warnings

For external use only.

Uses

Helps prevent and treat fungal skin infections; For the treatment of athlete’s foot (tinea pedis); For the treatment of ringworm (tinea corporis); Helps relieve itching, burning, redness, irritation, scaling, and discomfort associated with fungal infections; Helps prevent recurrence when used daily.

PACKAGE LABEL

Brand: Tuymec

Name: Antifungal Soap

Size: 4.1 oz (116g)x 2 Bars